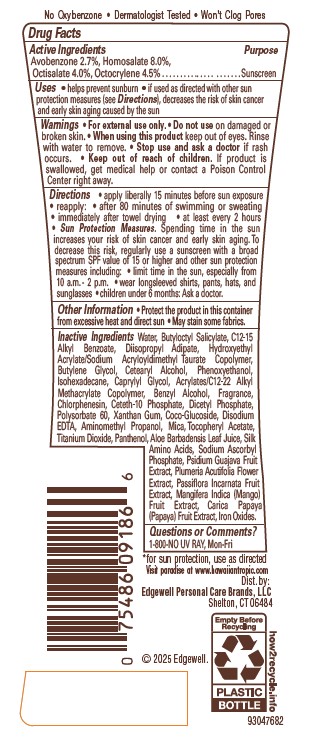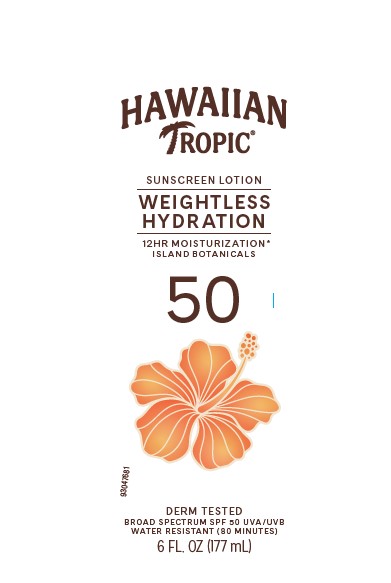 DRUG LABEL: HAWAIIAN TROPIC
NDC: 63354-512 | Form: LOTION
Manufacturer: Edgewell Personal Care Brands LLC
Category: otc | Type: HUMAN OTC DRUG LABEL
Date: 20250928

ACTIVE INGREDIENTS: AVOBENZONE 2.7 g/100 g; OCTISALATE 4.5 g/100 g; OCTOCRYLENE 5.2 g/100 g
INACTIVE INGREDIENTS: PASSIFLORA INCARNATA FRUIT; CHLORPHENESIN; XANTHAN GUM; SODIUM ASCORBYL PHOSPHATE; WATER; STARCH, RICE; DIISOPROPYL ADIPATE; DEHYDRATED ALCOHOL; GLYCERIN; PHENOXYETHANOL; ALOE VERA LEAF; GUAVA; PAPAYA; GLUCONOLACTONE; CORN OIL; EDETATE DISODIUM; BETA CAROTENE; CARBOMER HOMOPOLYMER, UNSPECIFIED TYPE; CAPRYLYL GLYCOL; ALPHA-TOCOPHEROL ACETATE; SAFFLOWER OIL; PLUMERIA RUBRA FLOWER; SODIUM HYDROXIDE; PANTHENOL; MANGO

Active Ingredients

Avobenzone 2.7%, Octisalate 4.5%, Octocrylene 5.2%

Purpose

Sunscreen

Uses

• helps prevent sunburn • if used as directed with other sun protection measures (see Directions), decreases the risk of skin cancer and early skin aging caused by the sun

Warnings

For external use only.

Do not use

on damaged or broken skin.

When using this product

keep out of eyes. Rinse with water to remove.

Stop use and ask a doctor

if rash occurs.

Keep out of reach of children.

If product is swallowed, get medical help or contact a Poison Control Center right away. • May stain some fabrics and surfaces.

Directions

• apply liberally 15 minutes before sun exposure • reapply: • after 80 minutes of swimming or sweating • immediately after towel drying • at least every 2 hours • Sun Protection Measures. Spending time in the sun increases your risk of skin cancer and early skin aging. To decrease this risk, regularly use a sunscreen with a broad spectrum SPF value of 15 or higher and other sun protection measures including: • limit time in the sun, especially from 10 a.m. - 2 p.m. • wear longsleeved shirts, pants, hats, and sunglasses • children under 6 months: Ask a doctor.

Inactive Ingredients

Water, Carthamus Tinctorius (Safflower) Seed Oil, Diisopropyl Adipate, Oryza Sativa (Rice) Starch, Glycerin, Acrylates/C12-22 Alkyl Methacrylate Copolymer, Alcohol Denat., Phenoxyethanol, Carbomer, Caprylyl Glycol, Sodium Hydroxide, Chlorphenesin, Fragrance, Gluconolactone, Xanthan Gum, Disodium EDTA, Tocopheryl Acetate, Panthenol, Aloe Barbadensis Leaf Juice, Zea Mays (Corn) Oil, Sodium Ascorbyl Phosphate, Beta-Carotene, Carica Papaya (Papaya) Fruit Extract, Mangifera Indica (Mango) Fruit Extract, Passiflora Incarnata Fruit Extract, Plumeria Acutifolia Flower Extract, Psidium Guajava Fruit Extract

Other Information

Protect this product from excessive heat and direct sun

Questions or Comments?

1-800-NO UV RAY, Mon-Fri

Principal Display Panel

HAWAIIAN TROPIC

SUNSCREEN LOTION

WEIGHTLESS

HYDRATION

12HR MOISTURIZATION*

ISLAND BOTANICALS

50

DERM TESYTED

BROAD SPECTRUM SPF 50 UVA/UVB

WATER RESISTANT (80 MINUTES)

6 FL. OZ. (177 mL)